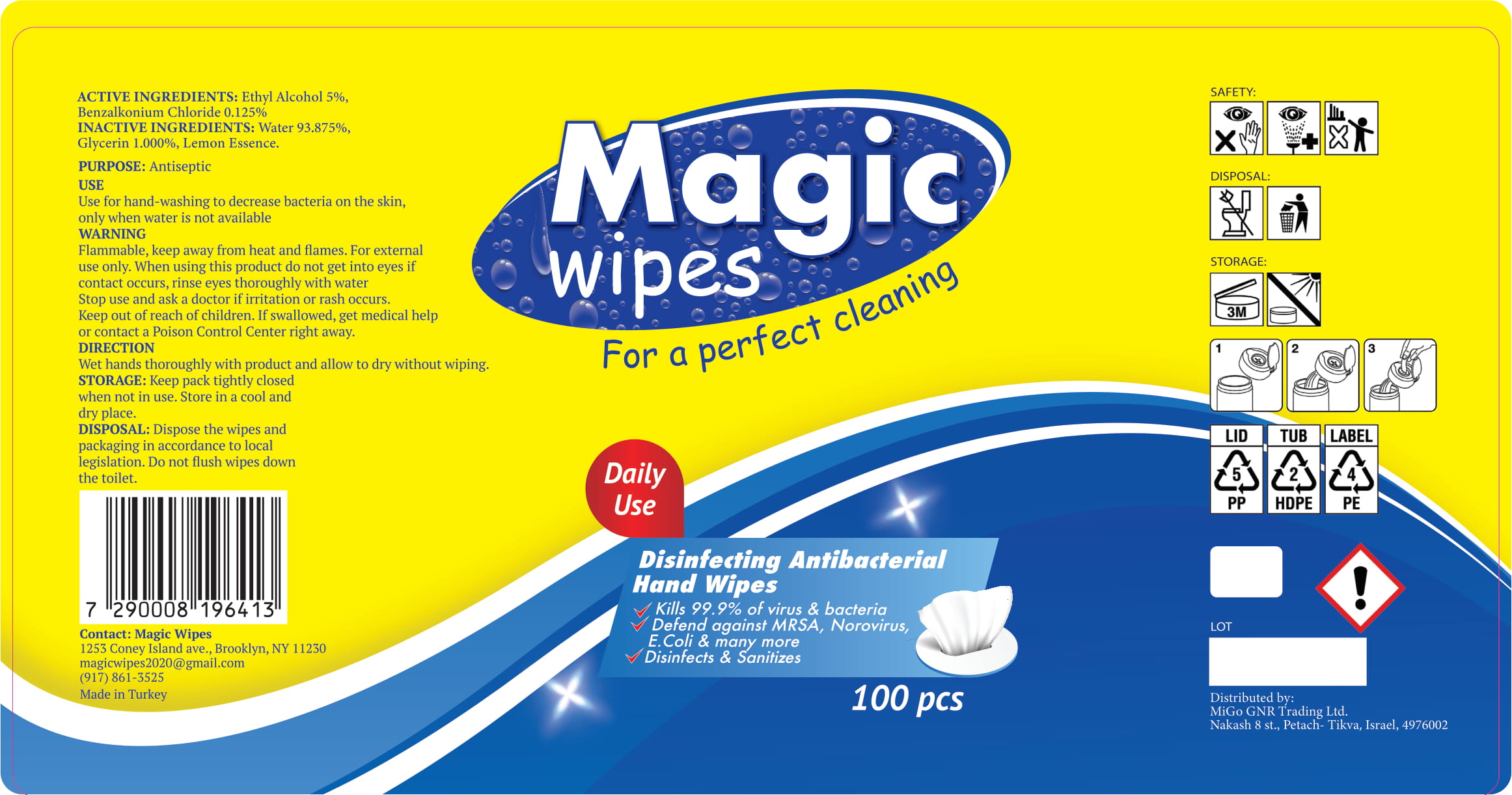 DRUG LABEL: Magic Wipes
NDC: 80840-001 | Form: CLOTH
Manufacturer: NATURE GENERATIONS SANAYI VE DIS TICARET LIMITED SIRKETI
Category: otc | Type: HUMAN OTC DRUG LABEL
Date: 20201006

ACTIVE INGREDIENTS: BENZALKONIUM CHLORIDE 0.125 g/100 g; ALCOHOL 5 g/100 g
INACTIVE INGREDIENTS: GLYCERIN; WATER

Active Ingredient(s)

Ethyl Alcohol 5%, Benzalkonium Chloride 0.125%

Purpose

Antiseptic

Use

Use for hand-washing to decrease bacteria on the skin, only when water is not available.

Warnings

Flammable. Keep away from heat and flames. For external use only.

When using this product do not get into eyes if contact occurs, rinse eyes thoroughly with water.

Stop use and ask a doctor if irritation or rash occurs.

Keep out of reach of children. If swallowed, get medical help or contact a Poison Control Center right away.

Directions

Wet hands thoroughly with the product and allow to dry without wiping.

Other information

Keep pack tightly closed when not in use. Store in a cool and dry place.

Inactive ingredients

Water 93.875%, Glycerin 1.000%, Lemon Essence.

Disposal

Dispose the wipes and packaging in accordance to local legislation. Do not flush wipes down the toilet.

Package Label - Principal Display Panel

Magic wipes

For a perfect cleaning

Daily Use

Disinfecting Antibacterial Hand Wipes

- Kills 99.9% of virus & bacteria
- Defend against MRSA, Norovirus, E. Coli & many more
- Disinfects & Sanitizes

Contact: Magic Wipes

1253 Coney Island ave. Brooklyn, NY 11230

magicwipes2020@gmail.com

(917) 861-3525

Made in Turkey

Distributed by:

MiGo GNR Trading Ltd.

Nakash 8 st., Petach-Tikva, Israel, 4976002